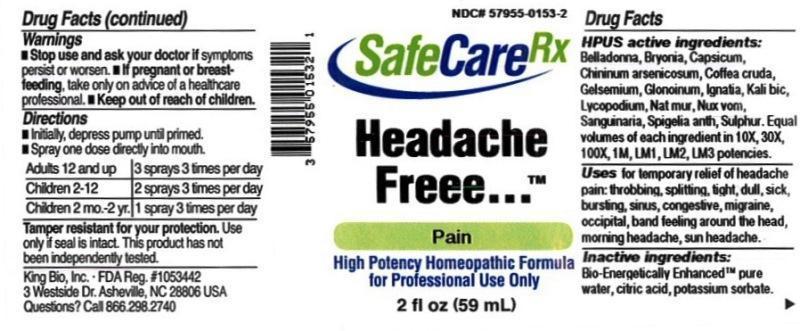 DRUG LABEL: Headache Freee
NDC: 57955-0183 | Form: LIQUID
Manufacturer: King Bio Inc.
Category: homeopathic | Type: HUMAN OTC DRUG LABEL
Date: 20180214

ACTIVE INGREDIENTS: ATROPA BELLADONNA 10 [hp_X]/59 mL; BRYONIA ALBA ROOT 10 [hp_X]/59 mL; CAPSICUM 10 [hp_X]/59 mL; QUININE ARSENITE 10 [hp_X]/59 mL; ARABICA COFFEE BEAN 10 [hp_X]/59 mL; GELSEMIUM SEMPERVIRENS ROOT 10 [hp_X]/59 mL; NITROGLYCERIN 10 [hp_X]/59 mL; STRYCHNOS IGNATII SEED 10 [hp_X]/59 mL; POTASSIUM DICHROMATE 10 [hp_X]/59 mL; LYCOPODIUM CLAVATUM SPORE 10 [hp_X]/59 mL; SODIUM CHLORIDE 10 [hp_X]/59 mL; STRYCHNOS NUX-VOMICA SEED 10 [hp_X]/59 mL; SANGUINARIA CANADENSIS ROOT 10 [hp_X]/59 mL; SPIGELIA ANTHELMIA 10 [hp_X]/59 mL; SULFUR 10 [hp_X]/59 mL
INACTIVE INGREDIENTS: WATER; CARYA OVATA BARK; CITRUS BIOFLAVONOIDS; LONICERA JAPONICA FLOWER; POLYEPSILON-LYSINE (4000 MW); REBAUDIOSIDE A

Headache Freee™

ACTIVE INGREDIENT

Drug Facts__________________________________________________________________________________________________________

HPUS active ingredients: Belladonna, Bryonia, Capsicum, Chininum arsenicosum, Coffea cruda, Gelsemium, Glonoinum, Ignatia, Kali bic, Lycopodium, Nat mur, Nux vom, Sanguinaria, Spigelia anth, Sulphur.

Equal volumes of each ingredient in 10X, 30X, 100X, 1LM, 2LM, 3LM, 5LM potencies.

INDICATIONS AND USAGE

Uses for temporary relief of headache pain: throbbing, splitting, tight, dull, sick, bursting, sinus, congestive, migraine, occipital.

Inactive Ingredients:

Bio-Energetically Enhanced™ pure water, Carya ovata bark extract, citrus extract, Lonicera japonica (honeysuckle), polylysine, steviol glycosides.

Warnings

- Stop use and ask your doctor if symptoms persist or worsen.
- If pregnant or breast-feeding, take only on advice of a healthcare professional.

- Keep out of reach of children.

Directions

- Initially, depress pump until primed.
- Spray one dose directly into mouth.
- Adults 12 and up: 3 sprays 3 times per day.
- Children 2-12: 2 sprays 3 times per day.
- Children 2 mo-2 yr: 1 spray 3 times per day.

OTHER SAFETY INFORMATION

Tamper resistant for your protection. Use only if safety seal is intact. This product has not been clinically tested.

PURPOSE

Uses for temporary relief of headache pain:

- throbbing
- splitting
- tight
- dull
- sick
- bursting
- sinus
- congestive
- migraine
- occipital